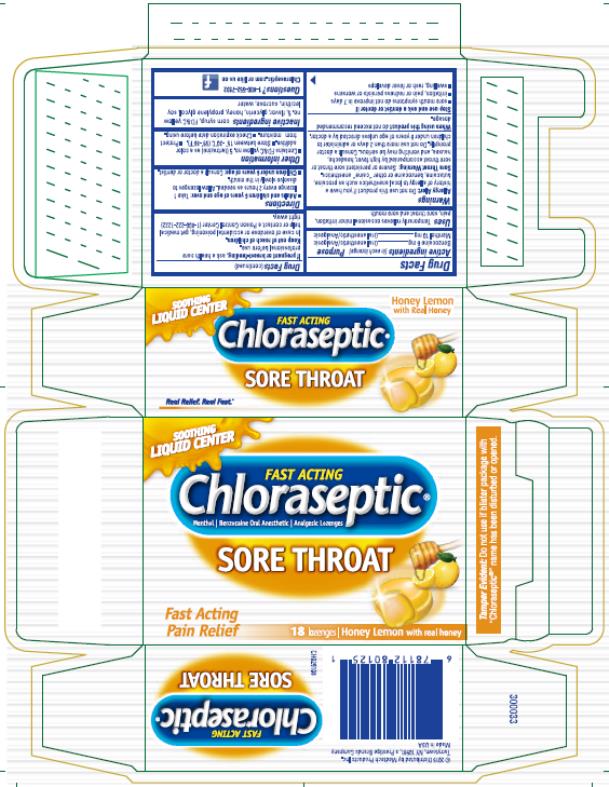 DRUG LABEL: Chloraspetic
NDC: 67172-023 | Form: LOZENGE
Manufacturer: Prestige Brands Holdings, Inc.
Category: otc | Type: HUMAN OTC DRUG LABEL
Date: 20241025

ACTIVE INGREDIENTS: MENTHOL 10 mg/1 1; BENZOCAINE 6 mg/1 1
INACTIVE INGREDIENTS: CORN SYRUP; FD&C YELLOW NO. 5; GLYCERIN; LECITHIN, SOYBEAN; SUCROSE; WATER; HONEY; PROPYLENE GLYCOL

Chloraseptic Honey Lemon Lozenge

Drug Facts

Active ingredients (in each lozenge)

Benzocaine 6 mg

Menthol 10 mg

Purpose

Oral pain reliever

Oral pain reliever

Uses

Temporarily relieves occasional minor irritation, pain, sore throat and sore mouth.

Warnings

Allergy Alert: do not use this product if you have a history of allergy to local anesthetics such as procaine, butacaine, benzocaine, or other “caine” anesthetics. If a skin reaction occurs, stop use and seek medical help right away.

Sore Throat Warning Severe or persistent sore throat or sore throat accompanied by high fever, headache, nausea, and vomiting may be serious. Consult a doctor promptly. Do not use more than 2 days or give to children under 6 years of age unless directed by a doctor.

Do not use

- for teething
- in children under 6 years of age

When using this product

do not exceed recommended dosage.

Stop use and ask a dentist or doctor if:

- sore mouth symptoms do not improve in 7 days
- irritation, pain or redness persists or worsens
- swelling, rash or fever develops

If pregnant or breast-feeding,

ask a health care professional before use.

Keep out of reach of children.

In case of overdose, get medical help or contact a Poison Control Center (1-800-222-1222) right away.

Directions

Adults and children 6 years of age and older: Take 1 lozenge every 2 hours as needed. Allow lozenges to dissolve slowly in the mouth.

Children under 6 years of age: Do not use.

Other information

- Contains FD&C yellow no. 5 (tartrazine) as a color additive.
- Store between 15○C - 30○C (59○F - 86○F)
- Protect from moisture.
- Check expiration date before using.

Inactive ingredients

corn syrup, FD&C yellow no. 5,, glycerin, honey, propylene glycol, soy lecithin, sucrose, water

Questions

1-800-552-7932 Chloraseptic.com

PRINCIPAL DISPLAY PANEL

Chloraseptic®

Sore throat

18 lozenges | Honey Lemon With real honey